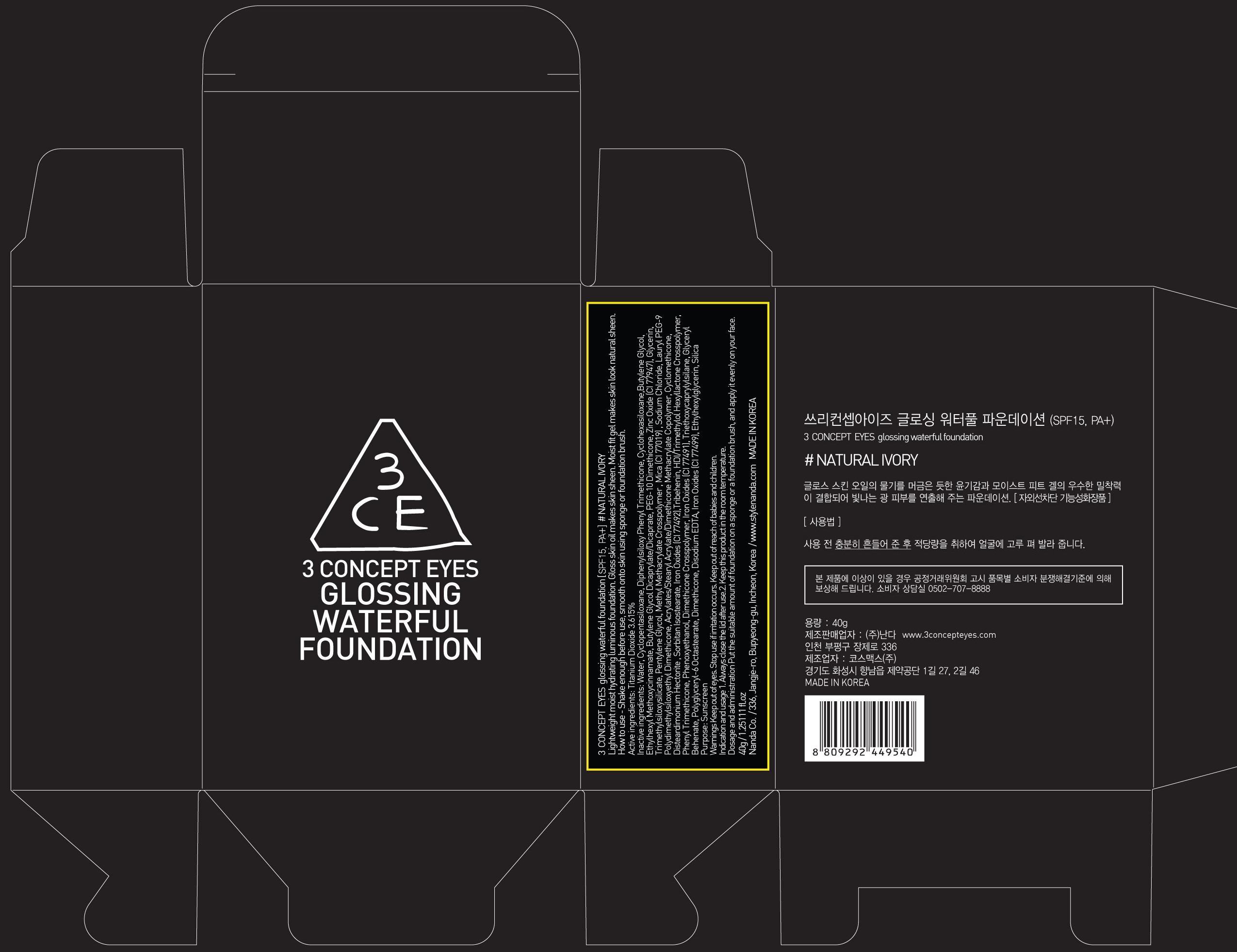 DRUG LABEL: 3 CONCEPT EYES GLOSSING WATERFUL FOUNDATION NATURAL IVORY
NDC: 60764-002 | Form: CREAM
Manufacturer: NANDA CO., LTD.
Category: otc | Type: HUMAN OTC DRUG LABEL
Date: 20131003

ACTIVE INGREDIENTS: Titanium Dioxide 1.44 g/40 g
INACTIVE INGREDIENTS: Water; Butylene Glycol

ACTIVE INGREDIENT

Active ingredients: Titanium Dioxide 3.615%

INACTIVE INGREDIENT

Inactive ingredients: Water, Cyclopentasiloxane, Diphenylsiloxy Phenyl Trimethicone, Cyclohexasiloxane, Butylene Glycol, Ethylhexyl Methoxycinnamate, Butylene Glycol Dicaprylate/Dicaprate, PEG-10 Dimethicone, Zinc Oxide (CI 77947), Glycerin, Trimethylsiloxysilicate, Pentylene Glycol, Methyl Methacrylate Crosspolymer , Mica (CI 77019) , Sodium Chloride, Lauryl PEG-9 Polydimethylsiloxyethyl Dimethicone, Acrylates/Stearyl Acrylate/Dimethicone Methacrylate Copolymer, Cyclomethicone, Disteardimonium Hectorite , Sorbitan Isostearate, Iron Oxides (CI 77492),Tribehenin, HDI/Trimethylol Hexyllactone Crosspolymer, Phenyl Trimethicone, Phenoxyethanol, Dimethicone Crosspolymer, Iron Oxides (CI 77491), Triethoxycaprylylsilane, Glyceryl Behenate, Polyglyceryl-6 Octastearate, Dimethicone, Disodium EDTA, Iron Oxides (CI 77499), Ethylhexylglycerin, Silica

PURPOSE

Purpose: Sunscreen

WARNINGS

Warnings: Keep out of eyes. Stop use if irritation occurs. Keep out of reach of babies and children.

KEEP OUT OF REACH OF CHILDREN

Keep out of reach of babies and children.

INDICATIONS AND USAGE

Indication and usage: 1. Always close the lid after use. 2. Keep this product in the room temperature.

Dosage and administration: Shake foundation enough to be mixed before use, and apply suitable amount of it on your face evenly with a foundation brush.